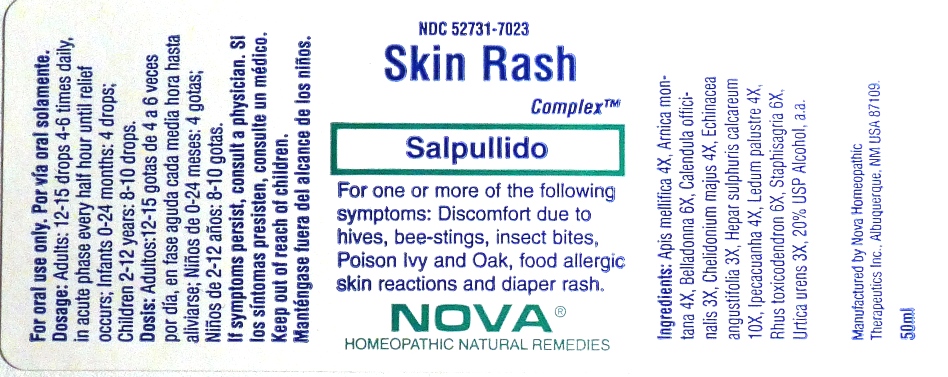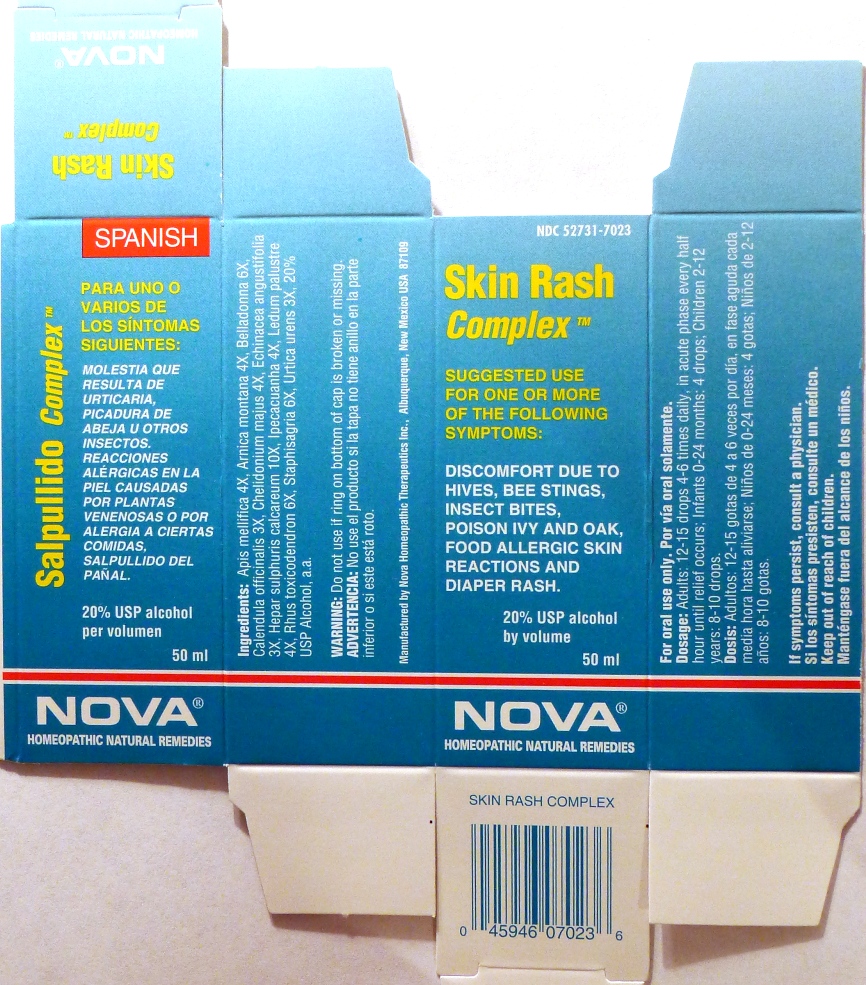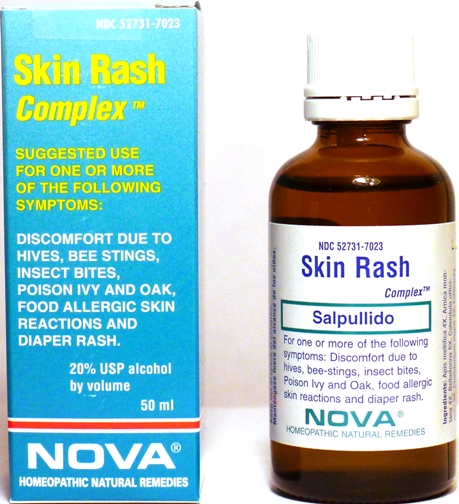 DRUG LABEL: Skin Rash Complex
NDC: 52731-7023 | Form: LIQUID
Manufacturer: Nova Homeopathic Therapeutics, Inc.
Category: homeopathic | Type: HUMAN OTC DRUG LABEL
Date: 20110601

ACTIVE INGREDIENTS: APIS MELLIFERA 4 [hp_X]/1 mL; ARNICA MONTANA 4 [hp_X]/1 mL; ATROPA BELLADONNA 6 [hp_X]/1 mL; CALENDULA OFFICINALIS FLOWERING TOP 3 [hp_X]/1 mL; CHELIDONIUM MAJUS 4 [hp_X]/1 mL; ECHINACEA ANGUSTIFOLIA 3 [hp_X]/1 mL; CALCIUM SULFIDE 10 [hp_X]/1 mL; IPECAC 4 [hp_X]/1 mL; LEDUM PALUSTRE TWIG 4 [hp_X]/1 mL; TOXICODENDRON PUBESCENS LEAF 6 [hp_X]/1 mL; DELPHINIUM STAPHISAGRIA SEED 6 [hp_X]/1 mL; URTICA URENS 3 [hp_X]/1 mL
INACTIVE INGREDIENTS: ALCOHOL

Skin Rash Complex

Purpose:

Suggested use for one or more of the following symptoms:

Discomfort due to hives, bee stings, insect bites, Poison Ivy and oak, food allergic skin reactions and diaper rash.

Usage and Dosage:

For oral use only.

DOSAGE AND ADMINISTRATION

Adults:
In Acute Phase:
12-15 drops, every half hour until relief occurs
When Relief Occurs:
12-15 drops, 4-6 times per day
Children 2-12 years:
8-10 drops, 4-6 times per day

Infants 0-24 months:
4 drops, 4-6 times per day

Warnings:

Keep out of reach of children.

WARNINGS

If symptoms persist, consult a physician.
Do not use if ring on bottom of cap is broken or missing.

Active Ingredients:

Apis mellifica 4X, Arnica montana 4X, Belladonna 6X, Calendula officinalis 3X, Chelidonium majus 4X, Echinacea angustifolia 3X, Hepar sulphuris calcareum 10X, Ipecacuanha 4X, Ledum palustre 4X, Rhus toxicodendron 6X, Staphisagria 6X, Urtica urens 3X

Inactive Ingredients:

Alcohol, 20% USP

QUESTIONS

Manufactured by Nova Homeopathic Therapeutics Inc., Albuquerque, New Mexico USA 87109
1-800-225-8094

PACKAGE LABEL

Skin Rash Complex Product
Skin Rash Complex Bottle Label
Skin Rash Complex Box